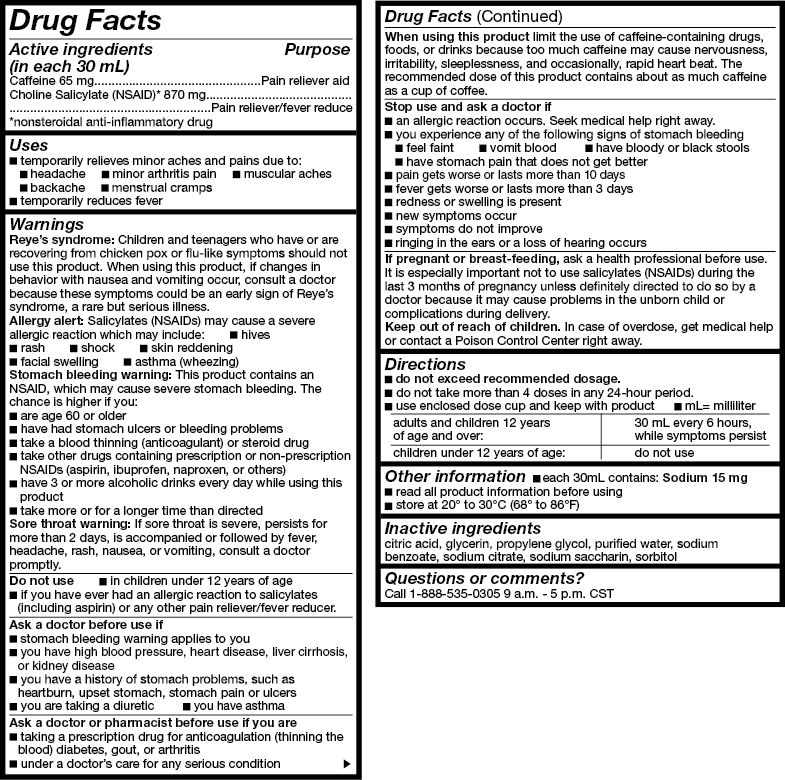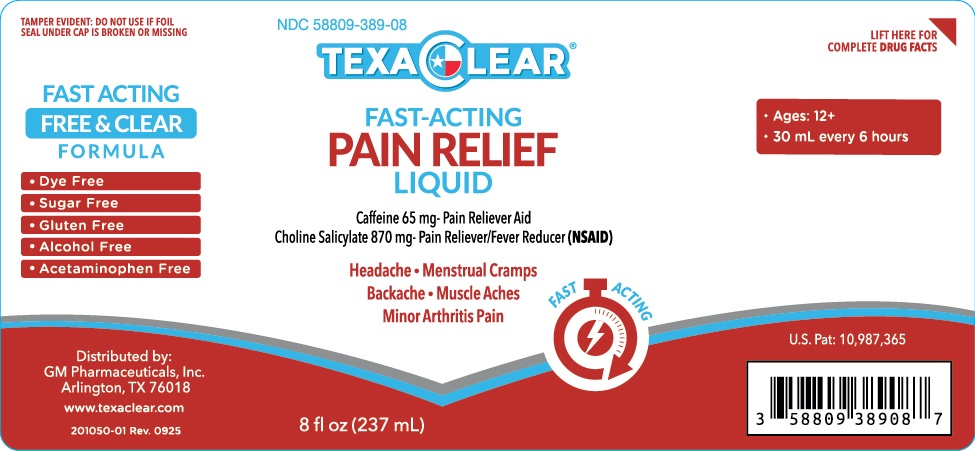 DRUG LABEL: TEXACLEAR PAIN RELIEVER
NDC: 58809-389 | Form: LIQUID
Manufacturer: GM Pharmaceuticals, INC
Category: otc | Type: HUMAN OTC DRUG LABEL
Date: 20251015

ACTIVE INGREDIENTS: CHOLINE SALICYLATE 870 mg/30 mL; CAFFEINE 65 mg/30 mL
INACTIVE INGREDIENTS: ANHYDROUS CITRIC ACID; GLYCERIN; PROPYLENE GLYCOL; WATER; SODIUM BENZOATE; SODIUM CITRATE; SACCHARIN SODIUM; SORBITOL

TEXACLEAR PAIN RELIEVER 8 oz

TEXACLEARPain Reliever

(choline salicylate&caffeine), solution

GM Pharmaceuticals, Inc.

--

TexaClear Pain Reliever Drug Facts

Drug Facts

Active Ingredients per 30mL

Caffeine 65 mg

Choline Salicylate (NSAID)* 870 mg

Purpose

Pain Reliever Aid

Pain Reliever / Fever Reducer (NSAID)

*nonsteroidal anti-inflammatory drug

Uses

- temporarily relieves minor aches and pains due to:
  ○ headache
  ○ minor arthritis pain
  ○ muscle aches
  ○ menstrual cramps
  ○ backache

- temporarily reduces fever

Warnings

Reye's syndrome

Children and teenagers who have or are recovering from chicken pox or flu-like symptoms should not use this product. When using this product, if changes in behavior with nausea and vomiting occur, consult a doctor because these symptoms could be an early sign of Reye's syndrome, a rare but serious illness.

Allergy alert

Salicylates (NSAIDs) may cause a severe allergic reaction which may include:

- hives
- skin reddening
- rash
- facial swelling
- shock
- asthma (wheezing)

Stomach bleedingwarning

This product contains an NSAID, which may cause severe stomach bleeding. The chance is higher if you:

- are age 60 or older
- have had stomach ulcers or bleeding problems
- take blood thinning (anticoagulant) or steroid drug
- take other drugs containing prescription or nonprescription NSAIDs (aspirin, ibuprofen, naproxen, or others)
- have 3 or more alcoholic drinks every day while using this product
- take more or for a longer time than directed

Do not use

- if you ever had an allergic reaction to salicylates (including aspirin) or any other pain reliever/ fever reducer.

Ask a doctor before use if

- stomach bleeding warning applies to you
- you have high blood pressure, heart disease, liver cirrhosis, or kidney disease
- you are taking a diuretic
- you have a history of stomach problems such as heartburn, upset stomach, stomach pain, or ulcers
- you have asthma

Ask a doctor or pharmacist before use if

- under a doctor's care for any serious condition
- taking a prescription drug for diabetes, gout, or arthritis.

When using this product

- limit the use of caffeine-containing medications, foods, or beverages because too much caffeine may cause nervousness, irritability, sleeplessness, and occasionally, rapid heart beat
- the recommended dose of this product contains about as much caffeine as a cup of coffee
- take with food or milk if stomach upset occurs

Stop use and ask a doctor if

- an allergic reaction occurs. Seek medical help right away.
- you experience any of the following signs of stomach bleeding:
  ○ feel faint
  ○ vomit blood
  ○ have bloody or black stools
  ○ have stomach pain that does not get better
- symptoms do not improve
- pain gets worse or lasts more than 10 days
- ringing in the ears or loss of hearing occurs
- redness or swelling is present
- new symptoms occur
- fever gets worse or lasts more than 3 days

If pregnant or breast-feeding,

ask a health professional before use. It is especially important not to use salicylates (NSAIDs) during the last 3 months of pregnancy unless definitely directed to do so by a doctor because it may cause problems in the unborn child or complications during delivery.

Keep out of reach of children.

In case of overdose, get medical help or contact a Poison Control Center right away.

Directions

- donot take more than directed.
- adults and children 12 years of age and over: take 30mL every 6 hours, while symptoms persist
- do not take exceed 4 doses in any 24 hours unless directed by a doctor
- children under 12 years of age: ask a doctor
- use enclosed dose cup

Other Information

- each 30mL contains: Sodium 19 mg
- read all product information before using
- store at room temperature 68-86ºF (20-30ºC)
- avoid excessive heat and humidity
- tamper evident: Do not use if foil seal under cap is broken or missing read all

Inactive Ingredients

anhydrous citric acid, glycerin, propylene glycol, purified water, sodium benzoate, sodium citrate, sodium saccharin, sorbitol

Questions or comments?

Call 1-888-423-0139

R071316M

PRINCIPAL DISPLAY PANEL

NDC 58809-389-08
TEXACLEAR
Pain
Reliever
8 fl oz (237 mL)